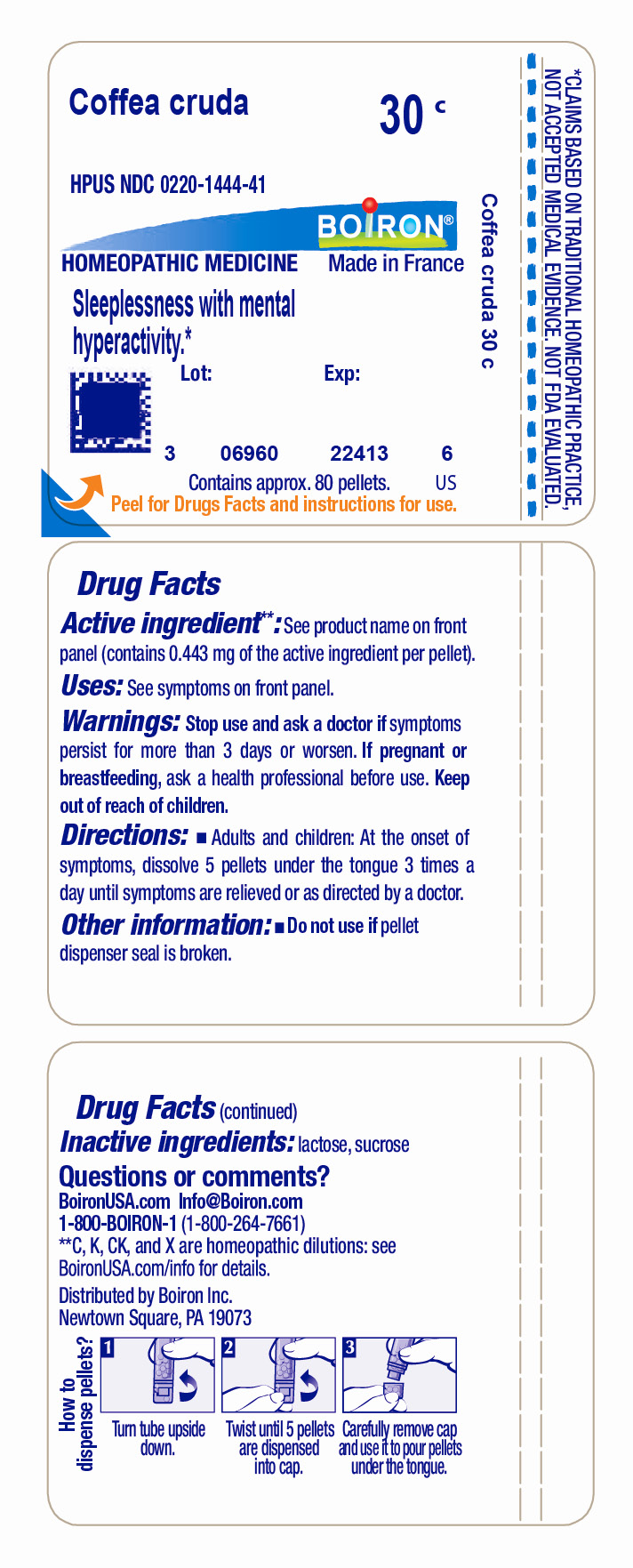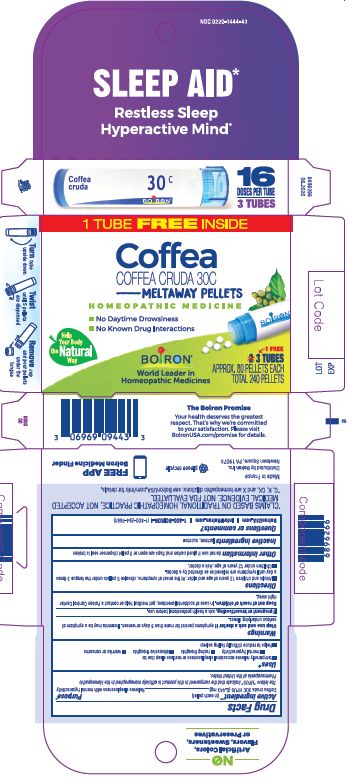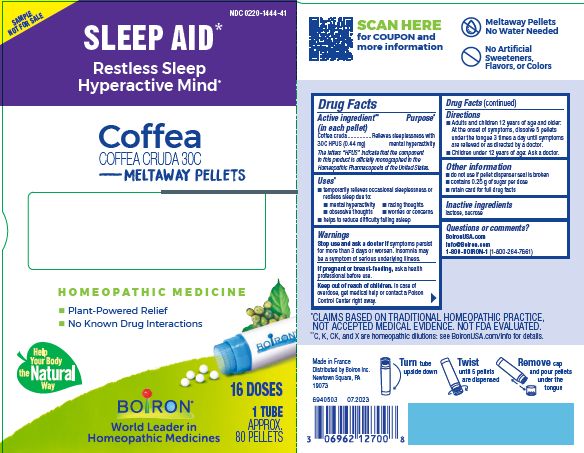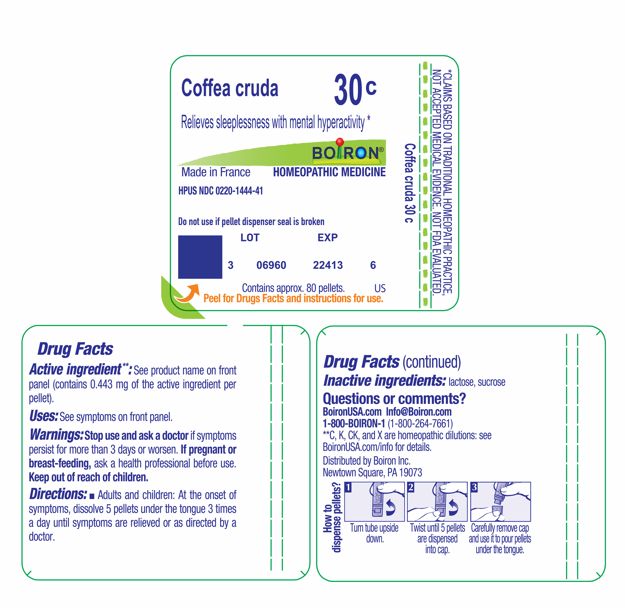 DRUG LABEL: Coffea cruda
NDC: 0220-1444 | Form: PELLET
Manufacturer: Boiron
Category: homeopathic | Type: HUMAN OTC DRUG LABEL
Date: 20251105

ACTIVE INGREDIENTS: ARABICA COFFEE BEAN 30 [hp_C]/30 [hp_C]
INACTIVE INGREDIENTS: LACTOSE, UNSPECIFIED FORM; SUCROSE

Coffea cruda 30C

Active ingredient**

Coffea cruda 30C HPUS (0.44 mg)

The letters "HPUS" indicate that the component in this product are officially monographed in the Homeopathic Pharmacopoeia of the United States.

PURPOSE

Coffea cruda 30C HPUS (0.44 mg) ... Relieves sleeplessness with mental hyperactivity

Uses*

temporarily relieves occasional sleeplessness or restless sleep due to:

- mental hyperactivity
- racing thoughts
- obsessive thoughts
- worries or concerns
- helps to reduce difficulty falling asleep

Stop use and ask a doctor if symptoms persist for more than 3 days or worsen. Insomnia may be a symptom of serious underlying illness.

PREGNANCY OR BREAST FEEDING

If pregnant or breast-feeding, ask a health professional before use.

Keep out of reach of children. In case of accidental overdose, get medical help or contact a Poison Control Center right away.

DOSAGE AND ADMINISTRATION

- Adults and children 12 years of age and older: At the onset of symptoms, dissolve 5 pellets under the tongue 3 times a day until symptoms are relieved or as directed by a doctor.
- Children under 12 years of age: Ask a doctor.

INACTIVE INGREDIENT

lactose, sucrose

QUESTIONS

BoironUSA.com

Info@Boiron.com

1-800-BOIRON-1 (1-800-264-7661)

Made in France

Distributed by Boiron, Inc.

Newtown Square, PA 19073

- do not use if pellet dispenser seal is broken
- contains 0.25 g of sugar per dose
- retain card for full drug facts

Turn tube upside down

Twist until 5 pellets are dispensed

Remove cap and pour pellets under the tongue

SLEEP AID*

Restless Sleep Hyperactive Mind*

3 TUBES

APPROX. 80 PELLETS EACH

TOTAL 240 PELLETS

1 TUBE

APPROX 80 PELLETS

No Daytime Drowsiness

No Known Drug Interactions

*CLAIMS BASED ON TRADITIONAL HOMEOPATHIC PRACTICE NOT ACCEPTED MEDICAL EVIDENCE. NOT FDA EVALUATED.
*C,K,CK, and X are homeopathic dilutions: see BoironUSA.com/info for details.